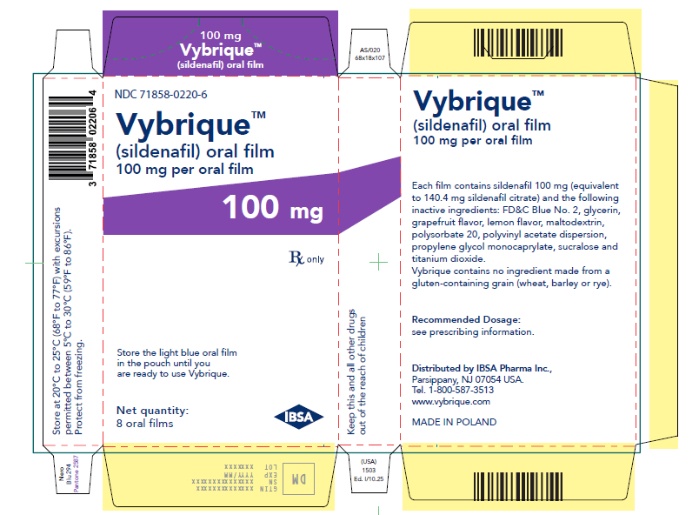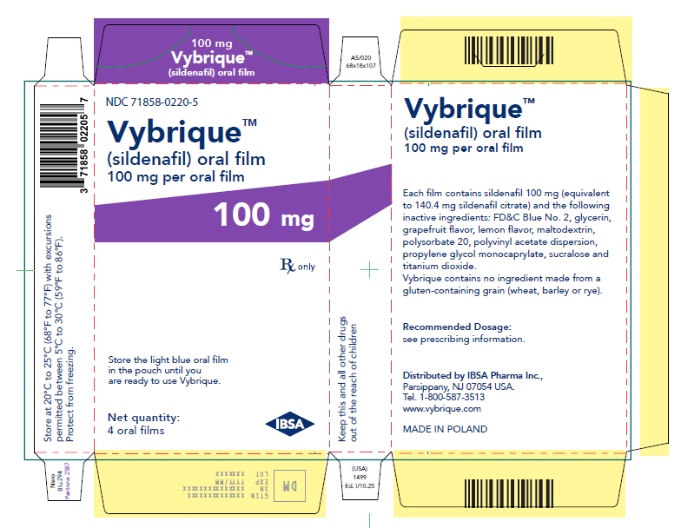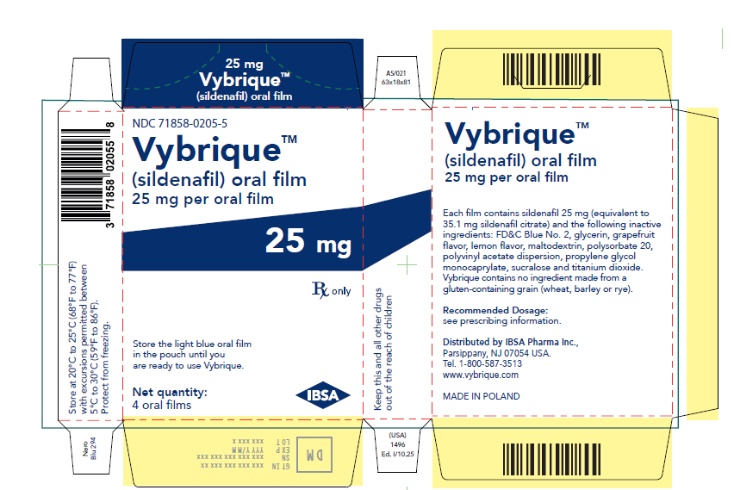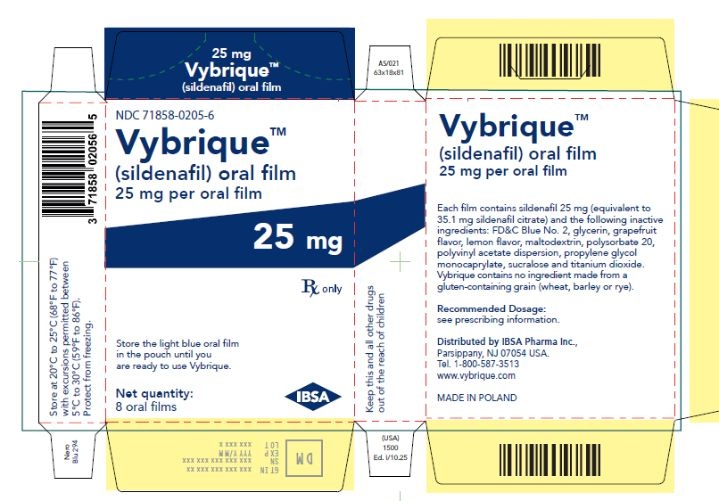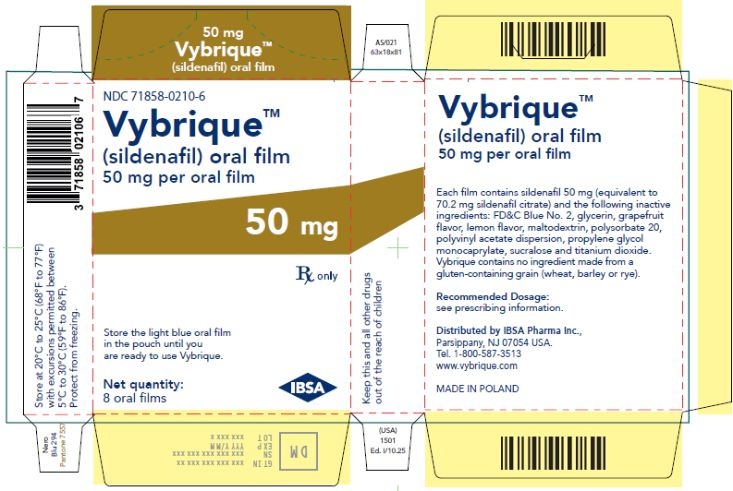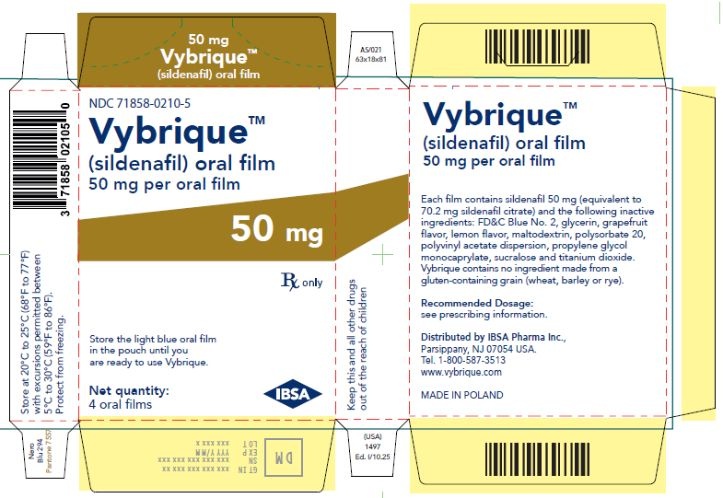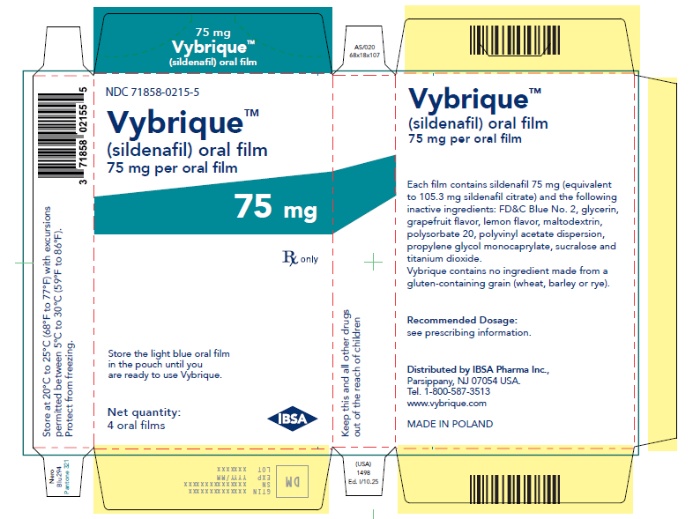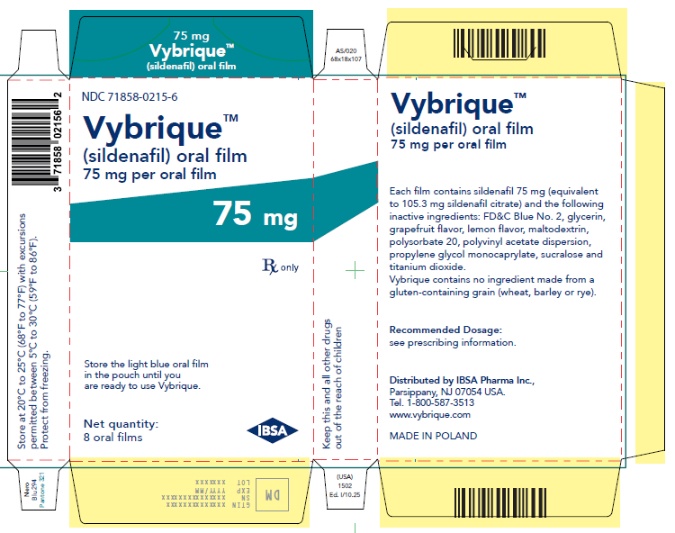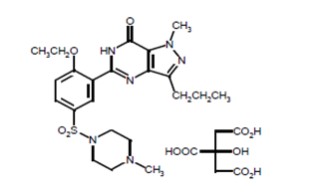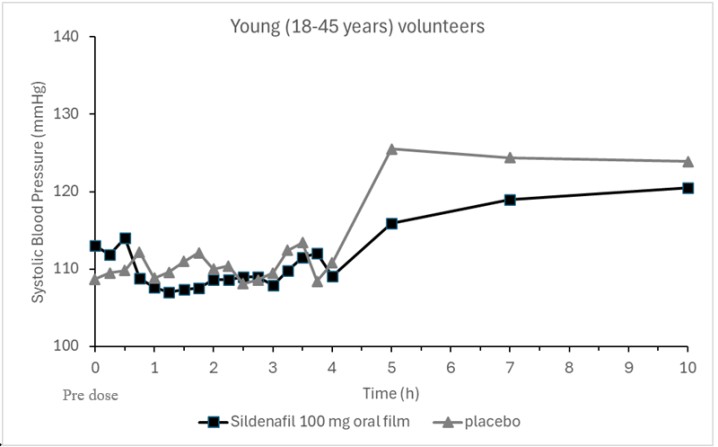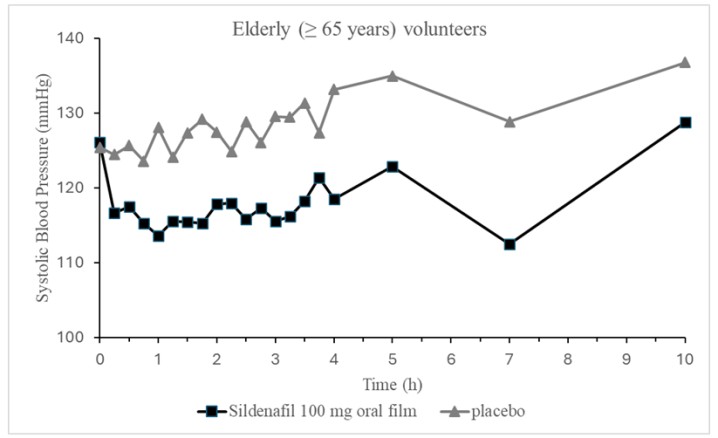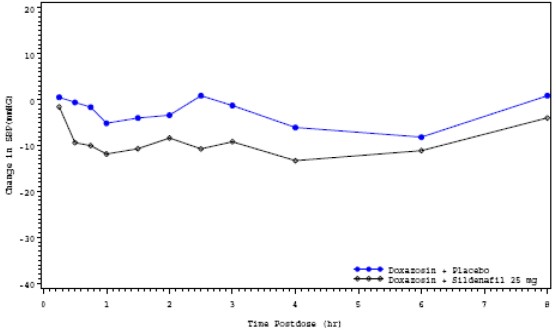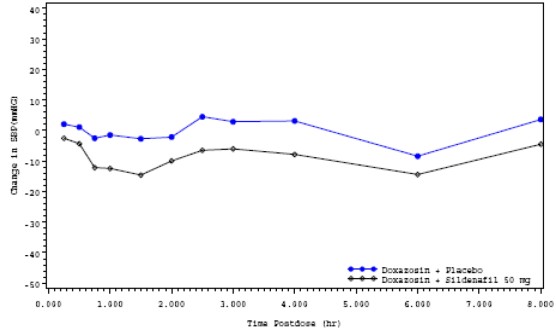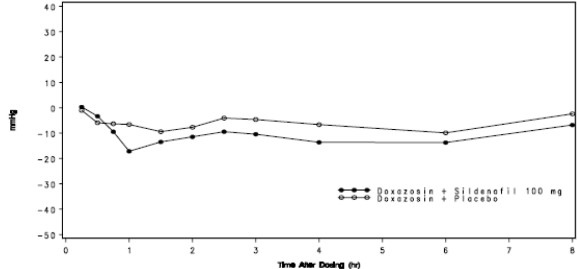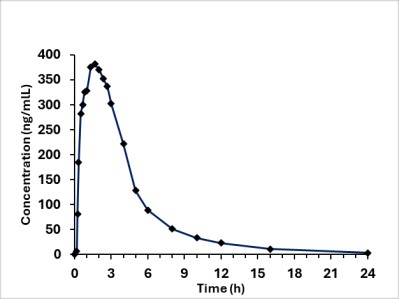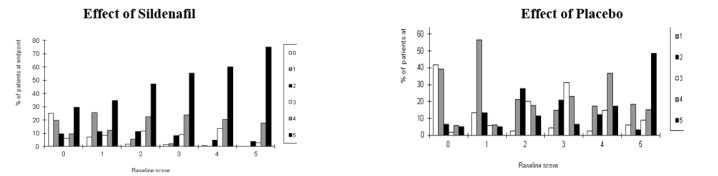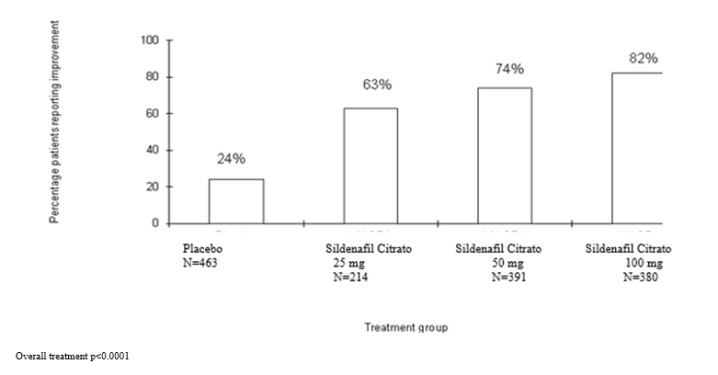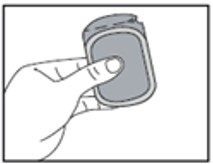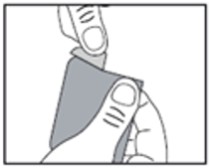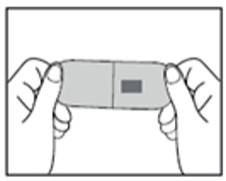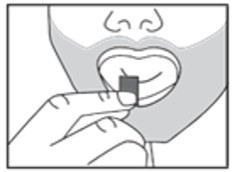 DRUG LABEL: Vybrique
NDC: 71858-0205 | Form: FILM
Manufacturer: IBSA Pharma Inc.
Category: prescription | Type: HUMAN PRESCRIPTION DRUG LABEL
Date: 20260226

ACTIVE INGREDIENTS: SILDENAFIL CITRATE 25 mg/1 1
INACTIVE INGREDIENTS: MALTODEXTRIN; GLYCERIN; PROPYLENE GLYCOL MONOCAPRYLATE; SUCRALOSE; POLYSORBATE 20; TITANIUM DIOXIDE; FD&C BLUE NO. 2

HIGHLIGHTS OF PRESCRIBING INFORMATION

These highlights do not include all the information needed to use VYBRIQUEsafely and effectively. See full prescribing information for VYBRIQUE.
VYBRIQUETM (sildenafil) oral film
Initial U.S. Approval:1998

1. INDICATIONSAND USAGE

VYBRIQUE is a phosphodiesterase-5 (PDE5) inhibitor indicated for the treatment of erectile dysfunction (ED). (1)

2. DOSAGE AND ADMINISTRATION

Dosage

- For most patients, the recommended dosage is 50 mg orally, taken as needed, approximately 1 hour before sexual activity. However, VYBRIQUE may be taken anywhere from 30 minutes to 4 hours before sexual activity. (2.1)
- Based on effectiveness and toleration, may increase to a maximum of 100 mg or decrease to 25 mg. (2.1)
- Maximum recommended dosing frequency is once per day. (2.1)
- Dosage Modifications for Drug Interactions: Refer to the full prescribing information for recommended dosage. (2.2)
- Recommended Dosage in Specific Populations: Refer to the full prescribing information for recommended dosage. (2.3)

Administration

- Administer with or without food.
- Place oral film directly onto the tongue where it will disintegrate and can then be swallowed with saliva without the need for water or other liquids.
- Do not cut or chew VYBRIQUE.

3. DOSAGE FORMS AND STRENGTHS

Oral film: 25 mg, 50 mg, 75 mg, 100 mg of sildenafil (3)

4. CONTRAINDICATIONS

- Administration of VYBRIQUE to patients using nitric oxide donors, such as organic nitrates or organic nitrites in any form. VYBRIQUE was shown to potentiate the hypotensive effect of nitrates. (4.1, 7.1, 12.2)
- Known hypersensitivity to sildenafil or any component of oral film. (4.2)
- Administration with guanylate cyclase (GC) stimulators, such as riociguat. (4.3)

5. WARNINGS AND PRECAUTIONS

- Patients should not use VYBRIQUE if sexual activity is inadvisable due to cardiovascular status. (5.1)
- Patients should seek emergency treatment if an erection lasts >4 hours.
- Use VYBRIQUE with caution in patients predisposed to priapism. (5.2)
- Patients should stop VYBRIQUE and seek medical care if a sudden loss of vision occurs in one or both eyes, which could be a sign of non-arteritic anterior ischemic optic neuropathy (NAION). VYBRIQUE should be used with caution, and only when the anticipated benefits outweigh the risks, in patients with a history of NAION. Patients with a “crowded” optic disc may also be at an increased risk of NAION. (5.3)
- Patients should stop VYBRIQUE and seek prompt medical attention in the event of sudden decrease or loss of hearing. (5.4)
- Caution is advised when VYBRIQUE is co-administered with alpha-blockers or antihypertensives. Concomitant use may lead to hypotension. (5.5)

- Decreased blood pressure, syncope, and prolonged erection may occur at higher sildenafil exposures. In patients taking strong CYP inhibitors such as ritonavir, sildenafil exposure is increased. Decrease in VYBRIQUE dosage is recommended. (2.2, 5.6)

6. ADVERSE REACTIONS

Most common adverse reactions (≥ 2%) include headache, flushing, dyspepsia, abnormal vision, nasal congestion, back pain, myalgia, nausea, dizziness and rash. (6.1)

To report SUSPECTED ADVERSE REACTIONS, contact IBSA Pharma Inc. at 1-800-587-3513 or FDA at 1-800-FDA-1088 or www.fda.gov/medwatch

7. DRUG INTERACTIONS

- VYBRIQUE can potentiate the hypotensive effects of nitrates, alpha blockers, and antihypertensives. (4.1, 5.5, 7.1, 7.2, 7.3, 12.2)
- With concomitant use of alpha blockers, initiate VYBRIQUE at 25 mg dose. (2.2)
- CYP3A4 inhibitors (e.g., ritonavir, ketoconazole, itraconazole, erythromycin) increase VYBRIQUE exposure. (2.2, 7.4, 12.3)
- Ritonavir: Do not exceed a maximum single dose of 25 mg in a 48- hour period. (2.2, 5.6)
- Erythromycin or strong CYP3A4 inhibitors (e.g., ketoconazole, itraconazole, saquinavir): Consider a starting dose of 25 mg. (2.2, 7.4)

8. USE IN SPECIFIC POPULATIONS

- Geriatric use: Recommended starting dose is 25 mg. (2.3, 8.5)
- Severe renal impairment: Recommended starting dose is 25 mg. (2.3, 8.6)
- Hepatic impairment: Recommended starting dose is 25 mg. (2.3, 8.7)

FULL PRESCRIBING INFORMATION

1. INDICATIONSAND USAGE

VYBRIQUETM is indicated for the treatment of erectile dysfunction.

2. DOSAGE AND ADMINISTRATION

2.1 Recommended Dosage

For most patients, the recommended dosage is 50 mg orally administered on the tongue, taken as needed, approximately 1 hour before sexual activity. However, VYBRIQUE may be taken anywhere from 30 minutes to 4 hours before sexual activity. The maximum recommended dosing frequency is once per day.

Based on effectiveness and tolerability the dosage may be increased to a maximum recommended dose of 100 mg or decreased to 25 mg, not to exceed once per day. For administration instructions, see Dosage and Administration (2.4).

2.2 Dosage Modificationsfor Drug Interactions

Nitrates

Concomitant use of nitrates in any form is contraindicated [see Contraindications (4.1), Drug Interactions (7.1) and Clinical Pharmacology (12.2)].

Alpha Blockers

Initiate VYBRIQUE at 25 mg orally in patients on concomitant therapy with an alpha-blocker. Patients should be stable on alpha-blocker therapy prior to initiating VYBRIQUE [see Warningsand Precautions (5.5), Drug Interactions (7.2), and Clinical Pharmacology (12.2)]. For administration instructions, see Dosageand Administration (2.4).

Ritonavir

The maximum recommended dose and dosing frequency is 25 mg orally taken once within a 48-hour period in ritonavir-treated patients. Concomitant administration of ritonavir increased the blood levels of sildenafil by 11-fold [see Warnings and Precautions (5.6), Drug Interactions (7.4), and Clinical Pharmacology (12.3)]. For administration instructions, see Dosage and Administration (2.4).

Other CYP3A4 Inhibitors

The recommended starting dosage is 25 mg orally, in patients taking strong CYP3A4 inhibitors (e.g., ketoconazole, itraconazole, or saquinavir) or erythromycin. Clinical data have shown that co-administration with saquinavir or erythromycin increased blood levels of sildenafil by about 3-fold [see Drug Interactions (7.4) and Clinical Pharmacology (12.3)]. For administration instructions, see Dosage and Administration (2.4).

2.3 Recommended Dosage in Specific Populations

Age Greater than 65 years

The recommended starting dosage is 25 mg orally in patients greater than 65 years of age [see Use in Specific Populations (8.5)]. For administration instructions, see Dosage and Administration (2.4).

Renal Impairment

The recommended starting dosage is 25 mg orally, in patients with severe renal impairment (creatinine clearance less than 30 mL/minute). The recommended starting dosage is 50 mg, in patients with mild (creatinine clearance 50 to 80 mL/min) and moderate (creatinine clearance 30 to 49 mL/min) renal impairment [see Use in Specific Populations(8.6) and Clinical Pharmacology (12.3)]. For administration instructions, see Dosage and Administration (2.4).

Hepatic Impairment

The recommended starting dosage is 25 mg orally in patients with any degree of hepatic impairment. In volunteers with mild and moderate degrees of hepatic impairment (Child-Pugh Class A and B), sildenafil clearance was reduced, resulting in higher plasma exposure of sildenafil (47% for Cmax and 85% for AUC), and the pharmacokinetics of sildenafil in patients with severe hepatic impairment (Child-Pugh Class C) have not been studied [see Use in Specific Populations (8.7) and Clinical Pharmacology (12.3)]. For administration instructions, see Dosage and Administration (2.4).

2.4 Important Administration Instructions

Administer VYBRIQUE orally with or without food. Place the oral film directly onto the tongue, where it will disintegrate and can then be swallowed with saliva without the need for water or other liquids. Do not cut or chew VYBRIQUE.

3. DOSAGE FORMS AND STRENGTHS

Oral Film:

- 25 mg sildenafil, opaque light blue, thin, flexible oral film imprinted with identification code S 25
- 50 mg sildenafil, opaque light blue, thin, flexible oral film imprinted with identification code S 50
- 75 mg sildenafil, opaque light blue, thin, flexible oral film imprinted with identification code S 75
- 100 mg sildenafil, opaque light blue, thin, flexible oral film imprinted with identification code S 100

4. CONTRAINDICATIONS

4.1 Nitrates

Consistent with its known effects on the nitric oxide/cGMP pathway [see Clinical Pharmacology (12.1,12.2)], VYBRIQUE potentiates the hypotensive effects of nitrates, and its administration to patients who are using nitric oxide donors such as organic nitrates or organic nitrites in any form either regularly and/or intermittently is therefore contraindicated.

After patients have taken VYBRIQUE it is unknown when nitrates, if necessary, can be safely administered. Although plasma levels of sildenafil at 24 hours post dose are much lower than at peak concentration, it is unknown whether nitrates can be safely co-administered at this time point [see Dosage and Administration (2.2), Drug Interactions (7.1), and Clinical Pharmacology (12.2)].

4.2 Hypersensitivity Reactions

VYBRIQUE is contraindicated in patients with a known hypersensitivity to sildenafil or any VYBRIQUE component. Hypersensitivity reactions, including rash and urticaria, have been reported [see Adverse Reactions (6.1)].

4.3 Concomitant Guanylate Cyclase (GC) Stimulators

Do not use VYBRIQUE in patients who are using a GC stimulator, such as riociguat. PDE5 inhibitors, including VYBRIQUE, may potentiate the hypotensive effects of GC stimulators.

5. WARNINGS AND PRECAUTIONS

5.1 Cardiovascular Risk

General

There is a potential for cardiac risk of sexual activity in patients with preexisting cardiovascular disease. Therefore, treatments for erectile dysfunction, including VYBIRQUE should not be used in men for whom sexual activity is inadvisable because of their underlying cardiovascular status.

The following groups of patients were not included in clinical safety and efficacy trials for sildenafil, and therefore, until further information is available, VYBRIQUE is not recommended for use in the following groups:

- Patients who have suffered a myocardial infarction, stroke, or life-threatening arrhythmia within the last 6 months
- Patients with resting hypotension (BP <90/50 mmHg) or hypertension (BP >170/110 mmHg)
- Patients with cardiac failure or coronary artery disease causing unstable angina.

Blood Pressure Decreases

Patients with left ventricular outflow obstruction (e.g., aortic stenosis, idiopathic hypertrophic subaortic stenosis) and those with severely impaired autonomic control of blood pressure can be sensitive to the actions of vasodilators, including VYBRIQUE.

As with other PDE5 inhibitors, VYBRIQUE has systemic vasodilatory properties that resulted in transient decreases in supine blood pressure in healthy volunteers. In healthy subjects aged 18 to 45 years, VYBRIQUE 100 mg resulted in mean maximal decreases relative to placebo of 6 mmHg systolic and 3 mmHg diastolic. In healthy subjects aged 65 years and older, VYBRIQUE 100 mg resulted in mean maximal decreases relative to placebo of 14 mmHg systolic and 8 mmHg diastolic [see Clinical Pharmacology (12.2)].

Prior to prescribing VYBRIQUE, carefully consider whether patients with underlying cardiovascular disease could be affected adversely by such vasodilatory effects, especially in combination with sexual activity.

5.2 Prolonged Erection and Priapism

Prolonged erection greater than 4 hours and priapism (painful erections greater than 6 hours in duration) have been reported infrequently since market approval of sildenafil. In the event of an erection that persists longer than 4 hours, instruct the patient to seek immediate medical assistance. If priapism is not treated immediately, penile tissue damage and permanent loss of potency could result.

Use VYBRIQUE with caution in patients with anatomical deformation of the penis (such as angulation, cavernosal fibrosis or Peyronie’s disease), or in patients who have conditions which may predispose them to priapism (such as sickle cell anemia, multiple myeloma, or leukemia).

5.3 Effects on the Eye

Advise patients to stop use of all phosphodiesterase type 5 (PDE5) inhibitors, including VYBRIQUE and seek medical attention in the event of a sudden loss of vision in one or both eyes. Such an event may be a sign of non-arteritic anterior ischemic optic neuropathy (NAION), a rare condition and a cause of decreased vision including permanent loss of vision, that has been reported rarely post-marketing in temporal association with the use of all PDE5 inhibitors. Based on published literature, the annual incidence of NAION is 2.5-11.8 cases per 100,000 in males aged 50 years and older.

An observational case-crossover study evaluated the risk of NAION when PDE5 inhibitor use, as a class, occurred immediately before NAION onset (within 5 half-lives), compared to PDE5 inhibitor use in a prior time period. The results suggest an approximate 2-fold increase in the risk of NAION, with a risk estimate of 2.15 (95% CI 1.06, 4.34). A similar study reported a consistent result, with a risk estimate of 2.27 (95% CI 0.99, 5.20). Other risk factors for NAION, such as the presence of “crowded” optic disc, may have contributed to the occurrence of NAION in these studies.

Neither the rare post-marketing reports, nor the association of PDE5 inhibitor use and NAION in the observational studies, substantiate a causal relationship between PDE5 inhibitor use and NAION [see Adverse Reactions (6.2)].

Consider whether patients with underlying NAION risk factors could be adversely affected by use of PDE5 inhibitors. Individuals who have already experienced NAION are at increased risk of NAION recurrence. Therefore, use PDE5 inhibitors, including VYBRIQUE with caution in these patients and only when the anticipated benefits outweigh the risks. Individuals with “crowded” optic disc are also considered at greater risk for NAION compared to the general population, however, evidence is insufficient to support screening of prospective users of PDE5 inhibitors, including VYBRIQUE, for this uncommon condition.

Patients with known hereditary degenerative retinal disorders, including retinitis pigmentosa, were not included in the sildenafil citrate clinical trials, and use in these patients is not recommended.

5.4 Sudden Hearing Loss

Advise patients to stop taking PDE5 inhibitors, including VYBRIQUE and seek prompt medical attention in the event of sudden decrease or loss of hearing. These events, which may be accompanied by tinnitus and dizziness, have been reported in temporal association to the intake of PDE5 inhibitors, including sildenafil. It is not possible to determine whether these events are related directly to the use of PDE5 inhibitors or to other factors [see Adverse Reactions (6.1,6.2)].

5.5 Hypotension when Co-administered with Alpha-blockers or Antihypertensives

Alpha-blockers

Caution is advised when PDE5 inhibitors are co-administered with alpha-blockers. PDE5 inhibitors, including sildenafil, and alpha-adrenergic blocking agents are both vasodilators with blood pressure lowering effects. When vasodilators are used in combination, an additive effect on blood pressure may occur. In some patients, concomitant use of these two drug classes can lower blood pressure significantly [see Drug Interactions (7.2) and Clinical Pharmacology (12.2)] leadingto symptomatic hypotension (e.g., dizziness, lightheadedness, fainting).

Consider the following:

- Patients should be stable on alpha-blocker therapy prior to initiating a PDE5 inhibitor. Patients who demonstrate hemodynamic instability on alpha-blocker therapy alone are at increased risk of symptomatic hypotension with concomitant use of PDE5 inhibitors.
- In patients who are stable on alpha-blocker therapy, PDE5 inhibitors should be initiated at the lowest dose [see Dosage and Administration (2.2)].
- In patients already taking an optimized dose of a PDE5 inhibitor, alpha-blocker therapy should be initiated at the lowest dose. Stepwise increase in alpha-blocker dose may be associated with further lowering of blood pressure when taking a PDE5 inhibitor.
- Safety of combined use of PDE5 inhibitors and alpha-blockers may be affected by other variables, including intravascular volume depletion and other antihypertensive drugs.

Antihypertensives

VYBRIQUE has systemic vasodilatory properties and may further lower blood pressure in patients taking antihypertensive medications.

When amlodipine, 5 mg or 10 mg, and sildenafil 100 mg were orally administered concomitantly to hypertensive patients, mean additional blood pressure reductions of 8 mmHg systolic and 7 mmHg diastolic were noted [see Drug Interactions (7.3) and Clinical Pharmacology (12.2) ].

5.6 Adverse Reactions with the Concomitant Use of Ritonavir

The concomitant administration of the protease inhibitor ritonavir substantially increases serum concentrations of sildenafil (11-fold increase in AUC). Data from subjects exposed to high systemic levels of sildenafil are limited. Decreased blood pressure, syncope, and prolonged erection were reported in some healthy volunteers exposed to high doses of sildenafil (200-800 mg). To decrease the chance of adverse reactions in patients taking ritonavir, the maximum recommended dosage and dosing frequency of VYBRIQUE is 25 mg once in a 48-hour period [see Dosage and Administration (2.2), Drug Interactions (7.4), and Clinical Pharmacology (12.3)].

5.7 Combination with other PDE5 Inhibitors or Other Erectile Dysfunction Therapies

The safety and efficacy of combinations of VYBRIQUE with other PDE5 inhibitors, including pulmonary arterial hypertension (PAH) treatments containing sildenafil or other treatments for erectile dysfunction, have not been studied. Such combinations may further lower blood pressure. Therefore, the use of such combinations is not recommended.

5.8 Effects on Bleeding

There have been postmarketing reports of bleeding events in patients who have taken sildenafil. A causal relationship between sildenafil and these events has not been established. In humans, sildenafil has no effect on bleeding time when taken alone or with aspirin. However, in vitro studies with human platelets indicate that sildenafil potentiates the antiaggregatory effect of sodium nitroprusside (a nitric oxide donor). In addition, the combination of heparin and sildenafil had an additive effect on bleeding time in the anesthetized rabbit, but this interaction has not been studied in humans.

The safety of sildenafil is unknown in patients with bleeding disorders and patients with active peptic ulceration.

5.9 Counseling Patients About Sexually Transmitted Diseases

The use of VYBRIQUE offers no protection against sexually transmitted diseases. Counseling of patients about the protective measures necessary to guard against sexually transmitted diseases, including the Human Immunodeficiency Virus (HIV), should be considered.

6. ADVERSE REACTIONS

The following are discussed in more detail in other sections of the labeling:

- Cardiovascular [see Warnings and Precautions (5.1)]
- Prolonged Erection and Priapism [see Warnings and Precautions (5.2)]
- Effects on the Eye [see Warnings and Precautions (5.3)]
- Hearing Loss [see Warnings and Precautions (5.4)]
- Hypotension when Co-administered with Alpha-blockers or Anti-hypertensives [see Warnings and Precautions (5.5)]
- Adverse Reactions with the Concomitant Use of Ritonavir [see Warnings and Precautions 5.6)]
- Combination with other PDE5 Inhibitors or Other Erectile Dysfunction Therapies [see Warnings and Precautions (5.7)]
- Effects on Bleeding [see Warnings and Precautions (5.8)]

The most common adverse reactions reported in clinical trials (≥ 2%) of sildenafil are headache, flushing, dyspepsia, abnormal vision, nasal congestion, back pain, myalgia, nausea, dizziness, and rash.

6.1 Clinical Trials Experience

Because clinical trials are conducted under widely varying conditions, adverse reaction rates observed in the clinical trials of a drug cannot be directly compared to rates in the clinical trials of another drug and may not reflect the rates observed in clinical practice.

Sildenafil was administered to over 3700 patients (aged 19-87 years) during pre-marketing clinical trials worldwide. Over 550 patients were treated for longer than one year.

In placebo-controlled clinical studies, the discontinuation rate due to adverse reactions for sildenafil (2.5%) was not significantly different from placebo (2.3%).

In fixed-dose studies, the incidence of some adverse reactions increased with dose. The type of adverse events in flexible-dose studies was similar to that for fixed dose studies. At doses above the recommended dose range, adverse reactions were similar to those detailed in Table 1 but generally were reported more frequently.

Table 1: Adverse Reactions Reported by ≥2% of Patients Treated with Sildenafil and More Frequent than Placebo in Fixed-Dose Clinical Studies
Adverse Reaction | 25 mg (n=312) | 50 mg (n=511) | 100 mg (n=506) | Placebo (n=607)
Headache | 16% | 21% | % 28 | % 7
Flushing | 10% | 19% | 18% | 2%
Dyspepsia | 3% | 9% | 17% | 2%
Abnormal vision† | 1% | 2% | 11% | 1%
Nasal congestion | 4% | 4% | 9% | 2%
Back pain | 3% | 4% | 4% | 2%
Myalgia | 2% | 2% | 4% | 1%
Nausea | 2% | 3% | 3% | 1%
Dizziness | 3% | 4% | 3% | 2%
Rash | 1% | 2% | 3% | 1%
†Abnormal Vision: Mild to moderate in severity and transient, predominantly color tinge to vision, but also increased sensitivity to light, or blurred vision.

When sildenafil was taken as recommended (on an as-needed basis) in flexible-dose, placebo-controlled clinical trials of two to twenty-six weeks duration, patients took sildenafil at least once weekly, and the following adverse reactions were reported:

Table 2 : Adverse Reactions Reported by ≥2% of Patients Treated with Sildenafil and More Frequent than Placebo in Flexible-Dose Clinical Studies
Adverse Reaction | Sildenafil N=734 | Placebo N=725
Headache | 16% | 4%
Flushing | 10% | 1%
Dyspepsia | 7% | 2%
Nasal Congestion | 4% | 2%
Abnormal Vision† | 3% | 0%
Back pain | 2% | 2%
Dizziness | 2% | 1%
Rash | 2% | 1%
†Abnormal Vision: Mild to moderate in severity and transient, predominantly color tinge to vision, but also increased sensitivity to light or blurred vision. In these studies, only one patient discontinued due to abnormal vision.

When VYBRIQUE was taken as recommended (on an as-needed basis) in a flexible-dose, placebo-controlled clinical trial of twelve weeks duration, patients took VYBRIQUE at least once weekly, not more than once per day, and the following adverse reactions were reported:

Table 3: Adverse Reactions Reported by ≥2% of Patients Treated with VYBRIQUE and More Frequent than Placebo in a Flexible-Dose Clinical Study
Adverse Reactions | VYBRIQUE N=354 | PLACEBO N=121
Headache | 11% | 4%
Flushing | 4% | 0%
Dyspepsia | 4% | 1%
Nasal Congestion | 3% | 0%
Dizziness | 2% | 0%

In this study, none of the patients discontinued due to adverse reactions to VYBRIQUE.

The following events occurred in <2% of patients in controlled clinical trials of sildenafil; a causal relationship to sildenafil is uncertain. Reported events include those with a plausible relation to drug use; omitted are minor events and reports too imprecise to be meaningful:

Body as a Whole:face edema, photosensitivity reaction, shock, asthenia, pain, chills, accidental fall, abdominal pain, allergic reaction, chest pain, accidental injury.

Cardiovascular:angina pectoris, AV block, migraine, syncope, tachycardia, palpitation, hypotension, postural hypotension, myocardial ischemia, cerebral thrombosis, cardiac arrest, heart failure, abnormal electrocardiogram, cardiomyopathy.

Digestive:vomiting, glossitis, colitis, dysphagia, gastritis, gastroenteritis, esophagitis, stomatitis, dry mouth, liver function tests abnormal, rectal hemorrhage, gingivitis.

Hemic and Lymphatic:anemia and leukopenia.

Metabolic and Nutritional:thirst, edema, gout, unstable diabetes, hyperglycemia, peripheral edema, hyperuricemia, hypoglycemic reaction, hypernatremia.

Musculoskeletal:arthritis, arthrosis, myalgia, tendon rupture, tenosynovitis, bone pain, myasthenia, synovitis.

Nervous:ataxia, hypertonia, neuralgia, neuropathy, paresthesia, tremor, vertigo, depression, insomnia, somnolence, abnormal dreams, reflexes decreased, hypesthesia.

Respiratory:asthma, dyspnea, laryngitis, pharyngitis, sinusitis, bronchitis, sputum increased, cough increased.

Skin and Appendages:urticaria, herpes simplex, pruritus, sweating, skin ulcer, contact dermatitis, exfoliative dermatitis.

Special Senses:sudden decrease or loss of hearing, mydriasis, conjunctivitis, photophobia, tinnitus, eye pain, ear pain, eye hemorrhage, cataract, dry eyes.

Urogenital:cystitis, nocturia, urinary frequency, breast enlargement, urinary incontinence, abnormal ejaculation, genital edema and anorgasmia.

Analysis of the safety database from sildenafil controlled clinical trials showed no apparent difference in adverse reactions in patients taking sildenafil with and without antihypertensive medication. This analysis was performed retrospectively and was not powered to detect any pre-specified difference in adverse reactions.

6.2 Postmarketing Experience

The following adverse reactions have been identified during post approval use of sildenafil. Because these reactions are reported voluntarily from a population of uncertain size, it is not always possible to reliably estimate their frequency or establish a causal relationship to drug exposure. These events have been chosen for inclusion either due to their seriousness, reporting frequency, lack of clear alternative causation, or a combination of these factors.

Cardiovascular and Cerebrovascular:serious cardiovascular, cerebrovascular, and vascular events, including myocardial infarction, sudden cardiac death, ventricular arrhythmia, cerebrovascular hemorrhage, transient ischemic attack, hypertension, subarachnoid and intracerebral hemorrhages, and pulmonary hemorrhage have been reported post-marketing in temporal association with the use of sildenafil. Most, but not all, of these patients had preexisting cardiovascular risk factors. Many of these events were reported to occur during or shortly after sexual activity, and a few were reported to occur shortly after the use of sildenafil without sexual activity. Others were reported to have occurred hours to days after the use of sildenafil and sexual activity. It is not possible to determine whether these events are related directly to sildenafil, to sexual activity, to the patient’s underlying cardiovascular disease, to a combination of these factors, or to other factors [see Warnings and Precautions (5.1) and Patient Counseling Information (17)].

Hemic and Lymphatic: vaso-occlusive crisis: In a small, prematurely terminated study of sildenafil in patients with pulmonary arterial hypertension (PAH) secondary to sickle cell disease, vaso-occlusive crises requiring hospitalization were more commonly reported in patients who received sildenafil than in those randomized to placebo. The clinical relevance of this finding to men treated with sildenafil for ED is not known.

Nervous:seizure, seizure recurrence, anxiety, and transient global amnesia.

Respiratory:epistaxis

Special senses:

Hearing:Cases of sudden decrease or loss of hearing have been reported postmarketing in temporal association with the use of PDE5 inhibitors, including sildenafil. In some of the cases, medical conditions and other factors were reported that may have also played a role in the otologic adverse events. In many cases, medical follow-up information was limited. It is not possible to determine whether these reported events are related directly to the use of sildenafil, to the patient’s underlying risk factors for hearing loss, a combination of these factors, or to other factors [see Warnings and Precautions (5.4), Patient Counseling Information (17)].

Ocular:diplopia, temporary vision loss/decreased vision, ocular redness or bloodshot appearance, ocular burning, ocular swelling/pressure, increased intraocular pressure, retinal edema, retinal vascular disease or bleeding, and vitreous traction/detachment.

Non-arteritic anterior ischemic optic neuropathy (NAION), a cause of decreased vision including permanent loss of vision, has been reported rarely post-marketing in temporal association with the use of phosphodiesterase type 5 (PDE5) inhibitors, including sildenafil. Most, but not all, of these patients had underlying anatomic or vascular risk factors for developing NAION, including but not necessarily limited to: low cup to disc ratio (“crowded disc”), age over 50, diabetes, hypertension, coronary artery disease, hyperlipidemia and smoking [see Warnings and Precautions (5.3), Patient Counseling Information (17)].

Urogenital: prolonged erection, priapism [see Warnings and Precautions (5.2) and Patient Counseling Information (17)],and hematuria.

7. DRUG INTERACTIONS

7.1 Nitrates

Administration of sildenafil with nitric oxide donors such as organic nitrates or organic nitrites in any form is contraindicated. Consistent with its known effects on the nitric oxide/cGMP pathway, sildenafil was shown to potentiate the hypotensive effects of nitrates [see Dosage and Administration (2.2), Contraindications (4.1), Clinical Pharmacology (12.2)] .

7.2 Alpha-blockers

Use caution when co-administering alpha-blockers with sildenafil because of potential additive blood pressure lowering effects. When sildenafil is co-administered with an alpha-blocker, patients should be stable on alpha blocker therapy prior to initiating sildenafil treatment and sildenafil should be initiated at the lowest dose [see Dosage and Administration (2.2),Warnings and Precautions (5.5), Clinical Pharmacology (12.2)].

7.3 Amlodipine

When sildenafil 100 mg was co-administered with amlodipine (5 mg or 10 mg) to hypertensive patients, the mean additional reduction on supine blood pressure was 8 mmHg systolic and 7 mmHg diastolic [see Warnings and Precautions (5.5), Clinical Pharmacology (12.2)].

7.4 Ritonavir and other CYP3A4 inhibitors

Co-administration of ritonavir, a strong CYP3A4 inhibitor, greatly increased the systemic exposure of sildenafil (11-fold increase in AUC). It is therefore recommended not to exceed a maximum single dose of 25 mg of sildenafil in a 48 hour period [see Dosage and Administration (2.2), Warnings and Precautions (5.6), Clinical Pharmacology (12.3)].

Co-administration of erythromycin, a moderate CYP3A4 inhibitor, resulted in 160% and 182% increases in sildenafil Cmax and AUC, respectively. Co-administration of saquinavir, a strong CYP3A4 inhibitor, resulted in 140% and 210% increases in sildenafil Cmax and AUC, respectively. Stronger CYP3A4 inhibitors such as ketoconazole or itraconazole could be expected to have greater effects than seen with saquinavir. A starting dose of 25 mg of sildenafil should be considered in patients taking erythromycin or strong CYP3A4 inhibitors (such as saquinavir, ketoconazole, itraconazole) [see Dosage and Administration (2.2), Clinical Pharmacology (12.3)].

7.5 Alcohol

In a drug-drug interaction study of sildenafil 50 mg given with alcohol 0.5 g/kg, in which mean maximum blood alcohol levels of 0.08% was achieved, sildenafil did not potentiate the hypotensive effect of alcohol in healthy volunteers [see Clinical Pharmacology (12.2)].

8. USE IN SPECIFIC POPULATIONS

8.1 Pregnancy

Risk Summary

VYBRIQUE is not indicated for use in females.

There are no data with the use of VYBRIQUE in pregnant women to inform any drug-associated risks for adverse developmental outcomes. Animal reproduction studies conducted with sildenafil did not show adverse developmental outcomes when administered during organogenesis in rats and rabbits at oral doses up to 16 and 32 times, respectively, the maximum recommended human dose (MRHD) of 100 mg/day on a mg/m2 basis (see Data).

Data

Animal Data

No evidence of teratogenicity, embryotoxicity or fetotoxicity was observed in rats and rabbits which received oral doses up to 200 mg/kg/day during organogenesis. These doses represent, respectively, about 16 and 32 times the MRHD on a mg/m2 basis in a 50 kg subject. In the rat pre- and postnatal development study, the no observed adverse effect dose was 30 mg/kg/day given for 36 days, about 2 times the MRHD on a mg/m2 basis in a 50 kg subject.

8.2 Lactation

Risk Summary

VYBRIQUE is not indicated for use in females.

Limited data indicate that sildenafil and its active metabolite are present in human milk. There is no information on the effects on the breastfed child, or the effects on milk production.

8.4 Pediatric Use

VYBRIQUE is not indicated for use in pediatric patients. Safety and effectiveness have not been established in pediatric patients.

8.5 Geriatric Use

Healthy elderly volunteers (65 years or over) had a reduced clearance of sildenafil resulting in approximately 84% and 107% higher plasma AUC values of sildenafil and its active N-desmethyl metabolite, respectively, compared to those seen in healthy young volunteers (18-45 years) [see Clinical Pharmacology (12.3)].Due to age-differences in plasma protein binding, the corresponding increase in the AUC of free (unbound) sildenafil and its active N-desmethyl metabolite were 45% and 57%, respectively [see Clinical Pharmacology (12.3)].

Of the total number of subjects in clinical studies of sildenafil, 18% were 65 years and older, while 2% were 75 years and older. No overall differences in safety or efficacy were observed between older (≥ 65 years of age) and younger adult (< 65 years of age) subjects.

Of the total number of subjects in the clinical study of VYBRIQUE, 31% were 65 years and older. No overall differences in safety or efficacy were observed between older (≥ 65 years of age) and younger (< 65 years of age) subjects.

A starting dose of VYBRIQUE 25 mg is recommended in patients 65 years of age and older due to the higher systemic exposure in older subjects, and larger decreases in blood pressure observed in older subjects in a clinical pharmacology study [see Dosage and Administration (2.3), Warnings and Precautions (5.1), Clinical Pharmacology (12.2].

8.6 Renal Impairment

No dose adjustment is required for mild (CLcr=50-80 mL/min) and moderate (CLcr=30-49 mL/min) renal impairment. In volunteers with severe renal impairment (Clcr<30 mL/min), sildenafil clearance was reduced, resulting in higher plasma exposure of sildenafil (~2 fold), approximately doubling of Cmax and AUC. A starting dose of 25 mg should be considered in patients with severe renal impairment [see Dosage and Administration (2.3), Clinical Pharmacology (12.3)].

8.7 Hepatic Impairment

In volunteers with hepatic impairment (Child-Pugh Class A and B), sildenafil clearance was reduced, resulting in higher plasma exposure of sildenafil (47% for Cmax and 85% for AUC). The pharmacokinetics of sildenafil in patients with severely impaired hepatic function (Child-Pugh Class C) have not been studied. A starting dose of 25 mg should be considered in patients with any degree of hepatic impairment [see Dosage and Administration (2.3), Clinical Pharmacology (12.3)].

10 OVERDOSAGE

In studies in healthy volunteers administered single sildenafil doses up to 800 mg, adverse reactions were similar to those seen at lower doses, but incidence rates and severities were increased.

In cases of overdose, standard supportive measures should be adopted as required. Renal dialysis is not expected to accelerate clearance as sildenafil is highly bound to plasma proteins and it is not eliminated in the urine.

11 DESCRIPTION

VYBRIQUE (sildenafil) oral film is for treatment of erectile dysfunction and contains sildenafil citrate, a selective inhibitor of cyclic guanosine monophosphate (cGMP)-specific phosphodiesterase type 5 (PDE5).

Sildenafil citrate is designated chemically as 1-[[3-(6,7-dihydro-1-methyl-7-oxo-3-propyl-1H-pyrazolo[4,3-d]pyrimidin-5-yl)-4-ethoxyphenyl]sulfonyl]-4-methylpiperazine citrate, has the molecular formula C22H39N6O4S ‧ C6H8O7, and the following structural formula:

Sildenafil citrate is a white to off-white crystalline powder with a solubility of 3.5 mg/mL in water and a molecular weight of 666.7.

VYBRIQUE is formulated as an opaque light blue, thin, flexible oral film with the characteristic lemon and grapefruit scent. The product is available in four different strengths 25, 50, 75, or 100 mg of sildenafil equivalent to 35, 70, 105, 140 mg sildenafil citrate respectively for oral administration. In addition to the active ingredient, sildenafil citrate, each oral film contains the following inactive ingredients: Blue Videojet ink, FD&C Blue No.2, glycerin, grapefruit flavor, lemon flavor, maltodextrin, polysorbate 20, polyvinyl acetate dispersion, propylene glycol monocaprylate, sucralose, titanium dioxide. VYBRIQUE contains no ingredient made from a gluten-containing grain (wheat, barley, or rye).

12 CLINICAL PHARMACOLOGY

12.1 Mechanism of Action

The physiologic mechanism of erection of the penis involves release of nitric oxide (NO) in the corpus cavernosum during sexual stimulation. NO then activates the enzyme guanylate cyclase, which results in increased levels of cyclic guanosine monophosphate (cGMP), producing smooth muscle relaxation in the corpus cavernosum and allowing inflow of blood.

Sildenafil enhances the effect of NO by inhibiting phosphodiesterase type 5 (PDE5), which is responsible for degradation of cGMP in the corpus cavernosum. Sildenafil has no direct relaxant effect on isolated human corpus cavernosum. When sexual stimulation causes local release of NO, inhibition of PDE5 by sildenafil causes increased levels of cGMP in the corpus cavernosum, resulting in smooth muscle relaxation and inflow of blood to the corpus cavernosum. Sildenafil at recommended doses has no effect in the absence of sexual stimulation.

Binding Characteristics

Studies in vitro have shown that sildenafil is selective for PDE5. Its effect is more potent on PDE5 than on other known phosphodiesterases (10-fold for PDE6, >80-fold for PDE1, >700-fold for PDE2, PDE3, PDE4, PDE7, PDE8, PDE9, PDE10, and PDE11). Sildenafil is approximately 4,000-fold more selective for PDE5 compared to PDE3. PDE3 is involved in control of cardiac contractility. Sildenafil is only about 10-fold as potent for PDE5 compared to PDE6, an enzyme found in the retina which is involved in the phototransduction pathway of the retina. This lower selectivity is thought to be the basis for abnormalities related to color vision [see Clinical Pharmacology (12.2)].

In addition to human corpus cavernosum smooth muscle, PDE5 is also found in other tissues including platelets, vascular and visceral smooth muscle, and skeletal muscle, brain, heart, liver, kidney, lung, pancreas, prostate, bladder, testis, and seminal vesicle. The inhibition of PDE5 in some of these tissues by sildenafil may be the basis for the enhanced platelet antiaggregatory activity of NO observed in vitro, an inhibition of platelet thrombus formation in vivo and peripheral arterial-venous dilatation in vivo.

12.2 Pharmacodynamics

Effects of Sildenafil on Erectile Response:In eight double-blind, placebo-controlled crossover studies of patients with either organic or psychogenic erectile dysfunction, sexual stimulation resulted in improved erections, as assessed by an objective measurement of hardness and duration of erections (RigiScan®), after sildenafil administration compared with placebo. Most studies assessed the efficacy of sildenafil approximately 60 minutes post dose. The erectile response, as assessed by RigiScan®, generally increased with increasing sildenafil dose and plasma concentration. The time course of effect was examined in one study, showing an effect for up to 4 hours but the response was diminished compared to 2 hours.

Effects of VYBRIQUE on Blood Pressure:

Single oral doses (50 mg, 75 mg, 100 mg) of VYBRIQUE administered to 12 healthy young volunteers produced decreases in supine blood pressure. The placebo-subtracted mean maximum decreases in systolic/diastolic blood pressure were 6.1/2.8 mmHg after a single 100 mg dose. Subjects were under fasting conditions and lay in the supine position for the first 4 hours post-dose and were not initially titrated. The decrease in supine blood pressure was most notable approximately 1-2 hours after dosing.

Figure 1: Mean Change from Baseline in Supine Systolic Blood Pressure, Healthy Volunteers

Single oral doses of 50 mg, 75 mg, 100 mg of VYBRIQUE administered to 12 elderly volunteers produced decreases in supine blood pressure. The placebo-subtracted maximum mean decreases in systolic/diastolic blood pressure were 13.7/8.5 mmHg after a single 100 mg dose. Subjects were under fasting conditions and lay in the supine position for the first 4 hours post-dose and were not initially titrated. The decrease in supine blood pressure was generally observed from 15 min to 4 h post-dose.

Figure 2: Mean Change from Baseline in Supine Systolic Blood Pressure, Elderly

Effects of Sildenafil on Blood Pressure When Nitroglycerin is Subsequently Administered:Based on the pharmacokinetic profile of a single 100 mg sildenafil oral dose given to healthy normal volunteers, the plasma levels of sildenafil at 24 hours post dose are approximately 2 ng/mL (compared to peak plasma levels of approximately 440 ng/mL). In the following patients: age >65 years, hepatic impairment (e.g., cirrhosis), severe renal impairment (e.g., creatinine clearance <30 mL/min), and concomitant use of erythromycin or strong CYP3A4 inhibitors, plasma levels of sildenafil at 24 hours post dose have been found to be 3 to 8 times higher than those seen in healthy volunteers. Although plasma levels of sildenafil at 24 hours post dose are much lower than at peak concentration, it is unknown whether nitrates can be safely co-administered at this time point [see Contraindications (4.1)].

Effects of Sildenafilon Blood Pressure When Co-administered with Alpha-Blockers:Three double-blind, placebo-controlled, randomized, two-way crossover studies were conducted to assess the interaction of sildenafil with doxazosin, an alpha-adrenergic blocking agent.

Study 1: Sildenafil with Doxazosin

In the first study, a single oral dose of sildenafil 100 mg or matching placebo was administered in a 2-period crossover design to 4 generally healthy males with benign prostatic hyperplasia (BPH). Following at least 14 consecutive daily doses of doxazosin, sildenafil 100 mg or matching placebo was administered simultaneously with doxazosin. Following a review of the data from these first 4 subjects (details provided below), the sildenafil dose was reduced to 25 mg. Thereafter, 17 subjects were treated with sildenafil 25 mg or matching placebo in combination with doxazosin 4 mg (15 subjects) or doxazosin 8 mg (2 subjects). The mean subject age was 66.5 years.

For the 17 subjects who received sildenafil 25 mg and matching placebo, the placebo-subtracted mean maximum decreases from baseline (95% CI) in systolic blood pressure were as follows:

Placebo-subtracted mean maximum decreasein systolic blood pressure (mm Hg) | Sildenafil 25 mg
Supine | 7.4 (-0.9 ,15.7)
Standing | 6.0 (-0.8, 12.8)

The mean profiles of the change from baseline in standing systolic blood pressure in subjects treated with doxazosin in combination with 25 mg sildenafil or matching placebo are shown in Figure 3.

Figure 3: Mean Standing Systolic Blood Pressure Change from Baseline

Blood pressure was measured immediately pre-dose and at 15, 30, 45 minutes, and 1, 1.5, 2, 2.5, 3, 4, 6 and 8 hours after sildenafil or matching placebo. Outliers were defined as subjects with a standing systolic blood pressure of <85 mmHg or a decrease from baseline in standing systolic blood pressure of >30 mmHg at one or more timepoints. There were no subjects treated with sildenafil 25 mg who had a standing SBP <85mmHg. There were three subjects with a decrease from baseline in standing systolic BP >30mmHg following sildenafil 25 mg, one subject with a decrease from baseline in standing systolic BP > 30 mmHg following placebo and two subjects with a decrease from baseline in standing systolic BP >30 mmHg following both sildenafil and placebo. No severe adverse events potentially related to blood pressure effects were reported in this group.

Of the four subjects who received sildenafil 100 mg in the first part of this study, a severe adverse event related to blood pressure effect was reported in one patient (postural hypotension that began 35 minutes after dosing with sildenafil with symptoms lasting for 8 hours), and mild adverse events potentially related to blood pressure effects were reported in two others (dizziness, headache and fatigue at 1 hour after dosing; and dizziness, lightheadedness and nausea at 4 hours after dosing). There were no reports of syncope among these patients. For these four subjects, the placebo-subtracted mean maximum decreases from baseline in supine and standing systolic blood pressures were 14.8 mmHg and 21.5 mmHg, respectively. Two of these subjects had a standing SBP <85mmHg. Both these subjects were protocol violators, one due to a low baseline standing SBP, and the other due to baseline orthostatic hypotension.

Study 2: Sildenafil with Doxazosin

In the second study, a single oral dose of sildenafil 50 mg or matching placebo was administered in a 2-period crossover design to 20 generally healthy males with BPH. Following at least 14 consecutive days of doxazosin, sildenafil 50 mg or matching placebo was administered simultaneously with doxazosin 4 mg (17 subjects) or with doxazosin 8 mg (3 subjects). The mean subject age in this study was 63.9 years.

Twenty subjects received sildenafil 50 mg, but only 19 subjects received matching placebo. One patient discontinued the study prematurely due to an adverse event of hypotension following dosing with sildenafil 50 mg. This patient had been taking minoxidil, a potent vasodilator, during the study.

For the 19 subjects who received both sildenafil and matching placebo, the placebo-subtracted mean maximum decreases from baseline (95% CI) in systolic blood pressure were as follows:

Placebo-subtracted mean maximum decrease in systolic blood pressure (mm Hg) | Sildenafil 50 mg (95% CI)
Supine | 9.08 (5.48, 12.68)
Standing | 11.62 (7.34, 15.90)

The mean profiles of the change from baseline in standing systolic blood pressure in subjects treated with doxazosin in combination with 50 mg sildenafil or matching placebo are shown in Figure 4.

Figure 4: Mean Standing Systolic Blood Pressure Change from Baseline

Blood pressure was measured after administration of sildenafil at the same times as those specified for the first doxazosin study. There were two subjects who had a standing SBP of <85 mmHg. In these two subjects, hypotension was reported as a moderately severe adverse event, beginning at approximately 1 hour after administration of sildenafil 50 mg and resolving after approximately 7.5 hours. There was one subject with a decrease from baseline in standing systolic BP >30mmHg following sildenafil 50 mg and one subject with a decrease from baseline in standing systolic BP >30 mmHg following both sildenafil 50 mg and placebo. There were no severe adverse events potentially related to blood pressure and no episodes of syncope reported in this study.

Study 3: Sildenafilwith Doxazosin

In the third study, a single oral dose of sildenafil 100 mg or matching placebo was administered in a 3-period crossover design to 20 generally healthy males with BPH. In dose period 1, subjects were administered open label doxazosin and a single dose of sildenafil 50 mg simultaneously, after at least 14 consecutive days of doxazosin. If a subject did not successfully complete this first dosing period, he was discontinued from the study. Subjects who had successfully completed the previous doxazosin interaction study (using sildenafil 50 mg), including no significant hemodynamic adverse events, were allowed to skip dose period 1. Treatment with doxazosin continued for at least 7 days after dose period 1. Thereafter, sildenafil 100 mg or matching placebo was administered simultaneously with doxazosin 4 mg (14 subjects) or doxazosin 8 mg (6 subjects) in standard crossover fashion. The mean subject age in this study was 66.4 years.

Twenty-five subjects were screened. Two were discontinued after study period 1: one failed to meet pre-dose screening qualifications and the other experienced symptomatic hypotension as a moderately severe adverse event 30 minutes after dosing with open-label sildenafil 50 mg. Of the twenty subjects who were ultimately assigned to treatment, a total of 13 subjects successfully completed dose period 1, and seven had successfully completed the previous doxazosin study (using sildenafil 50 mg).

For the 20 subjects who received sildenafil 100 mg and matching placebo, the placebo-subtracted mean maximum decreases from baseline (95% CI) in systolic blood pressure were as follows:

Placebo-subtracted mean maximum decrease in systolic blood pressure (mm Hg) | Sildenafil 100 mg
Supine | 7.9 (4.6, 11.1)
Standing | 4.3 (-1.8,10.3)

The mean profiles of the change from baseline in standing systolic blood pressure in subjects treated with doxazosin in combination with 100 mg sildenafil citrate or matching placebo are shown in Figure 5.

Figure 5: Mean Standing Systolic Blood Pressure Change from Baseline

Blood pressure was measured after administration of sildenafil at the same times as those specified for the previous doxazosin studies. There were three subjects who had a standing SBP of <85 mmHg. All three were taking sildenafil 100 mg, and all three reported mild adverse events at the time of reductions in standing SBP, including vasodilation and lightheadedness. There were four subjects with a decrease from baseline in standing systolic BP >30 mmHg following sildenafil 100 mg, one subject with a decrease from baseline in standing systolic BP >30 mmHg following placebo and one subject with a decrease from baseline in standing systolic BP >30 mmHg following both sildenafil citrate and placebo. While there were no severe adverse events potentially related to blood pressure reported in this study, one subject reported moderate vasodilatation after both sildenafil 50 mg and 100 mg. There were no episodes of syncope reported in this study.

Effect of Sildenafilon Blood Pressure When Co-administered with Antihypertensives:When sildenafil 100 mg oral was co-administered with amlodipine, 5 mg or 10 mg oral, to hypertensive patients, the mean additional reduction on supine blood pressure was 8 mmHg systolic and 7 mmHg diastolic.

Effect of Sildenafilon Blood Pressure When Co-administered with Alcohol:Sildenafil 50 mg did not potentiate the hypotensive effect of alcohol (0.5 g/kg) in healthy volunteers with mean maximum blood alcohol levels of 0.08%. The maximum observed decrease in systolic blood pressure was -18.5 mmHg when sildenafil was co-administered with alcohol versus -17.4 mmHg when alcohol was administered alone. The maximum observed decrease in diastolic blood pressure was -17.2 mmHg when sildenafil was co-administered with alcohol versus -11.1 mmHg when alcohol was administered alone. There were no reports of postural dizziness or orthostatic hypotension. The maximum recommended dose of 100 mg sildenafil was not evaluated in this study [see Drug Interactions (7.5)].

Effects of Sildenafil on Cardiac Parameters:Single oral doses of sildenafil up to 100 mg produced no clinically relevant changes in the ECGs of normal male volunteers.

Studies have produced relevant data on the effects of sildenafil citrate on cardiac output. In one small, open-label, uncontrolled, pilot study, eight patients with stable ischemic heart disease underwent Swan-Ganz catheterization. A total dose of 40 mg sildenafil was administered by four intravenous infusions.

The results from this pilot study are shown in Table 4; the mean resting systolic and diastolic blood pressures decreased by 7% and 10% compared to baseline in these patients. Mean resting values for right atrial pressure, pulmonary artery pressure, pulmonary artery occluded pressure and cardiac output decreased by 28%, 28%, 20% and 7% respectively. Even though this total dosage produced plasma sildenafil concentrations which were approximately 2 to 5 times higher than the mean maximum plasma concentrations following a single oral dose of 100 mg in healthy male volunteers, the hemodynamic response to exercise was preserved in these patients.

Table 4: Hemodynamic Data in Patients with Stable Ischemic Heart Disease after IntravenousAdministration of 40 mg of Sildenafil
Means ± SD | At rest |  |  |  | After 4 minutes of exercise
 | n | Baseline (B2) | n | Sildenafil (D1) | n | Baseline | n | Sildenafil
PAOP (mmHg) | 8 | 8.1 ± 5.1 | 8 | 6.5 ± 4.3 | 8 | 36.0 ± 13.7 | 8 | 27.8 ± 15.3
Mean PAP (mmHg) | 8 | 16.7 ± 4 | 8 | 12.1 ± 3.9 | 8 | 39.4 ± 12.9 | 8 | 31.7 ± 13.2
Mean RAP (mmHg) | 7 | 5.7 ± 3.7 | 8 | 4.1 ± 3.7 | - | - | - | -
Systolic SAP (mmHg) | 8 | 150.4 ± 12.4 | 8 | 140.6 ± 16.5 | 8 | 199.5 ± 37.4 | 8 | 187.8 ± 30.0
Diastolic SAP (mmHg) | 8 | 73.6 ± 7.8 | 8 | 65.9 ± 10 | 8 | 84.6 ± 9.7 | 8 | 79.5 ± 9.4
Cardiac output (L/min) | 8 | 5.6 ± 0.9 | 8 | 5.2 ± 1.1 | 8 | 11.5 ± 2.4 | 8 | 10.2 ± 3.5
Heart rate (bpm) | 8 | 67 ± 11.1 | 8 | 66.9 ± 12 | 8 | 101.9 ± 11.6 | 8 | 99.0 ± 20.4

In a double-blind study, 144 patients with erectile dysfunction and chronic stable angina limited by exercise, not receiving chronic oral nitrates, were randomized to a single dose of placebo or sildenafil 100 mg 1 hour prior to exercise testing. The primary endpoint was time to limiting angina in the evaluable cohort. The mean times (adjusted for baseline) to onset of limiting angina were 423.6 and 403.7 seconds for sildenafil (N=70) and placebo, respectively. These results demonstrated that the effect of sildenafil on the primary endpoint was statistically non-inferior to placebo.

Effects of Sildenafil on Vision:At single oral doses of 100 mg and 200 mg, transient dose-related impairment of color discrimination was detected using the Farnsworth-Munsell 100-hue test, with peak effects near the time of peak plasma levels. This finding is consistent with the inhibition of PDE6, which is involved in phototransduction in the retina. Subjects in the study reported this finding as difficulties in discriminating blue/green. An evaluation of visual function at doses up to twice the maximum recommended dose revealed no effects of sildenafil on visual acuity, intraocular pressure, or pupillometry.

Effects of Sildenafilon Sperm: There was no effect on sperm motility or morphology after single 100 mg oral doses of sildenafil in healthy volunteers.

12.3 Pharmacokinetics

Sildenafil is rapidly absorbed after oral administration, with a mean absolute bioavailability of 41% (range 25-63%). The pharmacokinetics of sildenafil are dose-proportional over the recommended dose range. It is eliminated predominantly by hepatic metabolism (mainly CYP3A4) and is converted to an active metabolite with properties similar to the parent, sildenafil. Both sildenafil and the metabolite have terminal half-lives of about 4 hours.

Figure 6: Mean Sildenafil Plasma Concentrations in Healthy Male Volunteers

Absorption and Distribution:VYBRIQUE is rapidly absorbed. Maximum observed plasma concentrations are reached within 30 to 300 minutes (median 80 minutes) of oral dosing in the fasted state. After a single dose of 100 mg of VYBRIQUE in adult males, the mean (coefficient of variation, %) peak plasma concentration (Cmax) and area under the concentration curve (AUC) of sildenafil were 503.5 (37.7%) ng/mL and 1902.4 (36.3%) ng·h/mL, respectively.

When VYBRIQUE is taken with a high fat meal, the rate of absorption is reduced, with a mean delay in Tmax of 87 minutes and a mean reduction in Cmax of 45%. AUC is not impacted by food.

In a clinical study in 35 healthy males (18-55 years old) where VYBRIQUE 100 mg was administered in fed conditions with or without water, no clinically significant differences in pharmacokinetics of sildenafil and its major N-desmethyl metabolite was observed.

The mean steady state volume of distribution (Vss) for sildenafil is 105 L, indicating distribution into the tissues. Sildenafil and its major circulating N-desmethyl metabolite are both approximately 96% bound to plasma proteins. Protein binding is independent of total drug concentrations.

Based upon measurements of sildenafil in semen of healthy volunteers 90 minutes after dosing, less than 0.001% of the administered dose may appear in the semen of patients.

Metabolism and Excretion:Sildenafil is cleared predominantly by the CYP3A4 (major route) and CYP2C9 (minor route) hepatic microsomal isoenzymes. The major circulating metabolite results from N-desmethylation of sildenafil and is itself further metabolized. This metabolite has a PDE selectivity profile similar to sildenafil and an in vitropotency for PDE5 approximately 50% of the parent drug. Plasma concentrations of this metabolite are approximately 40% of those seen for sildenafil, so that the metabolite accounts for about 20% of sildenafil’s pharmacologic effects.

After either oral or intravenous administration, sildenafil is excreted as metabolites predominantly in the feces (approximately 80% of administered oral dose) and to a lesser extent in the urine (approximately 13% of the administered oral dose). Similar values for pharmacokinetic parameters were seen in normal volunteers and in the patient population, using a population pharmacokinetic approach.

Pharmacokinetics in Special Populations

Geriatrics:Healthy elderly volunteers (65 years or over) had a reduced clearance of sildenafil, resulting in approximately 84% and 107% higher plasma AUC values of sildenafil and its active N-desmethyl metabolite, respectively, compared to those seen in healthy younger volunteers (18-45 years). Due to age-differences in plasma protein binding, the corresponding increase in the AUC of free (unbound) sildenafil and its active N-desmethyl metabolite were 45% and 57%, respectively [see Dosage and Administration (2.3), and Use in Specific Populations (8.5)]

Renal Impairment:In volunteers with mild (CLcr=50-80 mL/min) and moderate (CLcr=30-49 mL/min) renal impairment, the pharmacokinetics of a single oral dose of sildenafil (50 mg) were not altered. In volunteers with severe (CLcr <30 mL/min) renal impairment, sildenafil clearance was reduced, resulting in approximately doubling of AUC and Cmax compared to age-matched volunteers with no renal impairment [see Dosage and Administration (2.3), and Use in Specific Populations (8.6)].

In addition, N-desmethyl metabolite AUC and Cmax values significantly increased by 200% and 79%, respectively in subjects with severe renal impairment compared to subjects with normal renal function.

Hepatic Impairment:In volunteers with hepatic impairment (Child-Pugh Class A and B), sildenafil clearance was reduced, resulting in increases in AUC (85%) and Cmax (47%) compared to age-matched volunteers with no hepatic impairment. The pharmacokinetics of sildenafil in patients with severely impaired hepatic function (Child-Pugh Class C) have not been studied [see Dosage and Administration (2.3), and Use in Specific Populations (8.7)].

Therefore, age >65, hepatic impairment and severe renal impairment are associated with increased plasma levels of sildenafil. A starting oral dose of 25 mg should be considered in those patients [see Dosage and Administration (2.3)].

Drug Interaction Studies

Effects of Other Drugs on Sildenafil

Sildenafil metabolism is principally mediated by CYP3A4 (major route) and CYP2C9 (minor route). Therefore, inhibitors of these isoenzymes may reduce sildenafil clearance and inducers of these isoenzymes may increase sildenafil clearance. The concomitant use of erythromycin or strong CYP3A4 inhibitors (e.g., saquinavir, ketoconazole, itraconazole) as well as the nonspecific CYP inhibitor, cimetidine, is associated with increased plasma levels of sildenafil [see Dosage and Administration (2.2)].

In vivostudies:

Cimetidine (800 mg), a nonspecific CYP inhibitor, caused a 56% increase in plasma sildenafil concentrations when co-administered with sildenafil (50 mg) to healthy volunteers.

When a single 100 mg dose of sildenafil was administered with erythromycin, a moderate CYP3A4 inhibitor, at steady state (500 mg bid for 5 days), there was a 160% increase in sildenafil Cmax and an 182% increase in sildenafil AUC. In addition, in a study performed in healthy male volunteers, co-administration of the HIV protease inhibitor saquinavir, also a CYP3A4 inhibitor, at steady state (1200 mg tid) with sildenafil (100 mg single dose) resulted in a 140% increase in sildenafil Cmax and a 210% increase in sildenafil AUC. Sildenafil had no effect on saquinavir pharmacokinetics. A stronger CYP3A4 inhibitor such as ketoconazole or itraconazole could be expected to have greater effect than that seen with saquinavir. Population pharmacokinetic data from patients in clinical trials also indicated a reduction in sildenafil clearance when it was co-administered with CYP3A4 inhibitors (such as ketoconazole, erythromycin, or cimetidine) [see Dosage and Administration (2.2) and Drug Interactions (7.4)].

In another study in healthy male volunteers, co-administration with the HIV protease inhibitor ritonavir, which is a highly potent P450 inhibitor, at steady state (500 mg bid) with sildenafil (100 mg single dose) resulted in a 300% (4-fold) increase in sildenafil Cmax and a 1000% (11-fold) increase in sildenafil plasma AUC. At 24 hours the plasma levels of sildenafil were still approximately 200 ng/mL, compared to approximately 5 ng/mL when sildenafil was dosed alone. This is consistent with ritonavir’s marked effects on a broad range of P450 substrates. Sildenafil had no effect on ritonavir pharmacokinetics [see Dosage and Administration (2.2) and Drug Interactions (7.4)].

Although the interaction between other protease inhibitors and sildenafil has not been studied, their concomitant use is expected to increase sildenafil levels.

In a study of healthy male volunteers, co-administration of sildenafil at steady state (80 mg t.i.d.) with endothelin receptor antagonist bosentan (a moderate inducer of CYP3A4, CYP2C9 and possibly of CYP2C19) at steady state (125 mg b.i.d.) resulted in a 63% decrease of sildenafil AUC and a 55% decrease in sildenafil Cmax. Concomitant administration of strong CYP3A4 inducers, such as rifampin, is expected to cause greater decreases in plasma levels of sildenafil.

Single doses of antacid (magnesium hydroxide/aluminum hydroxide) did not affect the bioavailability of sildenafil citrate.

In healthy male volunteers, there was no evidence of a clinically significant effect of azithromycin (500 mg daily for 3 days) on the systemic exposure of sildenafil or its major circulating metabolite.

Pharmacokinetic data from patients in clinical trials showed no effect on sildenafil pharmacokinetics of CYP2C9 inhibitors (such as tolbutamide, warfarin), CYP2D6 inhibitors (such as selective serotonin reuptake inhibitors, tricyclic antidepressants), thiazide and related diuretics, ACE inhibitors, and calcium channel blockers. The AUC of the active metabolite, N-desmethyl sildenafil, was increased 62% by loop and potassium-sparing diuretics and 102% by nonspecific beta-blockers. These effects on the metabolite are not expected to be of clinical consequence.

Effects of Sildenafilon Other Drugs

In vitrostudies:

Sildenafil is a weak inhibitor of the CYP isoforms 1A2, 2C9, 2C19, 2D6, 2E1 and 3A4 (IC50 >150 μM). Given sildenafil peak plasma concentrations of approximately 1 μM after recommended doses, it is unlikely that sildenafil will alter the clearance of substrates of these isoenzymes.

In vivo studies:

No significant interactions were shown with tolbutamide (250 mg) or warfarin (40 mg), both of which are metabolized by CYP2C9.

In a study of healthy male volunteers, sildenafil (100 mg) did not affect the steady state pharmacokinetics of the HIV protease inhibitors, saquinavir and ritonavir, both of which are CYP3A4 substrates.

Sildenafil (50 mg) did not potentiate the increase in bleeding time caused by aspirin (150 mg).

Sildenafil at steady state, at a dose not approved for the treatment of erectile dysfunction (80 mg t.i.d.) resulted in a 50% increase in AUC and a 42% increase in Cmax of bosentan (125 mg b.i.d.).

13 NONCLINICAL TOXICOLOGY

13.1 Carcinogenesis, Mutagenesis, Impairment of Fertility

Carcinogenesis

Sildenafil was not carcinogenic when administered to rats for 24 months at a dose resulting in total systemic drug exposure (AUCs) for unbound sildenafil and its major metabolite of 20- and 38- times, for male and female rats, respectively, the exposures observed in human males given the Maximum Recommended Human Dose (MRHD) of 100 mg. Sildenafil was not carcinogenic when administered to mice for 18-21 months at dosages up to the Maximum Tolerated Dose (MTD) of 10 mg/kg/day, approximately 0.4 times the MRHD on a mg/m^2basis in a 50 kg subject.

Mutagenesis

Sildenafil was negative in in vitrobacterial and Chinese hamster ovary cell assays to detect mutagenicity, and invitrohuman lymphocytes and in vivomouse micronucleus assays to detect clastogenicity.

Impairment of Fertility

There was no impairment of fertility in rats given sildenafil up to 60 mg/kg/day for 36 days to females and 102 days to males, a dose producing an AUC value of more than 25 times the human male AUC.

14 CLINICAL STUDIES

Efficacy Results in VYBRIQUEClinical Study

The efficacy of VYBRIQUE in the treatment of erectile dysfunction was established in part on the basis of efficacy data from trials with the tablet formulation of sildenafil.

VYBRIQUE was evaluated in one randomized, double-blind, placebo-controlled, flexible-dose study (25 mg, 50 mg, 75 mg, 100 mg) over 12 weeks study to evaluate the erectile function of men with erectile dysfunction (ED). The co-primary efficacy endpoints included both a 4-week assessment of sexual function based on the International Index of Erectile Function (IIEF) questionnaire and an assessment of sexual function after each sexual intercourse based on the Sexual Encounter Profile (SEP) on the daily diary.

- The six-item, 30-point, erectile function (EF) domain of the IIEF was assessed at baseline, at follow-up visits, and at the end of the study reflecting subjects’ sexual experience during the past 4 weeks.
- The SEP Question 2 (“Were you able to insert your penis into your partner’s vagina”) and Question 3 (“Did your erection last long enough for you to have successful intercourse?”) were answered immediately after each sexual attempt with binary response (Yes=success, No=failure).

Sexual function data were recorded by patients in a daily diary.

A total of 475 patients were enrolled and received treatment with VYBRIQUE, including subjects with comorbidities such as diabetes, dyslipidemia, hypertension and obesity. Of these, 354 patients received VYBRIQUE and 121 patients received placebo without regard to food and alcohol concomitant intake. The initial dose was 50 mg for subjects under 65 years and 25 mg for subjects 65 years or older with dose adjustment permitted up to 50 mg (for subjects 65 years or older), 75 mg or 100 mg or down to 25 mg based on efficacy and tolerability. By the end of the study, 94 (26.6%) and 115 (32.5%) patients in the VYBRIQUE group were receiving 75 mg or 100 mg respectively. The efficacy of VYBRIQUE, administered at flexible doses of 25 mg, 50 mg, 75 mg and 100 mg for the treatment of ED, was superior to placebo. Efficacy results are shown in Figure 6. Subgroup analyses by age, race, and ethnicity showed efficacy results consistent with the overall population.

Table 5: Co-Primary Efficacy Results in a Randomized, Double-Blind, Placebo-Controlled, Flexible-Dose Study of VYBRIQUE
 | IIEF-EF Domain Score Mean (SD) |  | SEP Q2 Percentage (%) of ‘Yes’ Responses Mean (SD) |  | SEP Q3 Percentage (%) of ‘Yes’ Responses Mean (SD)
 | Sildenafil (N=354) | Placebo (N=121) | Sildenafil (N=354) | Placebo (N=121) | Sildenafil (N=354) | Placebo (N=121)
Baseline | 12.9 (4.8) | 12.7 (4.8) | 42.7 (34.3) | 44.2 (36.5) | 11.5 (17.2) | 8.9 (16.0)
Week 12 | 24.3 (6.6) | 21.0 (8.7) | 82.1 (28.8) | 68.6 (36.5) | 69.7 (34.2) | 49.9 (38.7)
Change from Baseline | 11.5 (7.1) | 8.2 (8.9) | 39.5 (35.3) | 24.2 (36.2) | 58.2 (34.6) | 41.3 (39.6)
Sildenafil - Placebo | IIEF-EF |  | SEP Q2 |  | SEP Q3
LS Means [95% CI] | 3.3* [1.6, 5.0] |  | 13.9%* [7.9%, 19.9%] |  | 19.0%* [11.8%, 26.3%]
*Statistically significant differences vs. placebo; p-value <0.001

IIEF= International Index of Erectile Function, EF = Erectile Function, SEP Q2=Sexual Encounter Profile Question 2, SEP Q3 = Sexual Encounter Profile Question 3, N = Number of Subjects, SD = Standard Deviation, LS = Least Squares, CI = Confidence Interval.

Sildenafil was assessed in many clinical studies for its effect on the ability of men with ED to engage in sexual activity and in many cases specifically on the ability to achieve and maintain an erection sufficient for satisfactory sexual activity. Sildenafil was evaluated primarily at doses of 25 mg, 50 mg and 100 mg in 21 randomized, double-blind, placebo-controlled trials of up to 6 months in duration, using a variety of study designs (fixed dose, titration, parallel, crossover). Sildenafil was administered to more than 3,000 patients aged 19 to 87 years, with ED of various etiologies (organic, psychogenic, mixed) with a mean duration of 5 years. sildenafil citrate demonstrated statistically significant improvement compared to placebo in all 21 studies. The studies that established benefit demonstrated improvements in success rates for sexual intercourse compared with placebo.

Sildenafil Efficacy Results from Controlled Clinical Studies

The effect of sildenafil on one of the major end points, maintenance of erections after penetration, is shown in Figure 7, for the pooled results of 5 sildenafil fixed-dose, dose-response studies of greater than one-month duration, showing response according to baseline function. Results with all doses have been pooled, but scores showed greater improvement at the 50 and 100 mg doses than at the 25 mg dose. The pattern of responses was similar for the other principal question, the ability to achieve an erection sufficient for intercourse. The titration studies, in which most patients received 100 mg, showed similar results. Figure 7 shows that regardless of the baseline levels of function, subsequent function in patients treated with sildenafil was better than that seen in patients treated with placebo. At the same time, on-treatment function was better in treated patients who were less impaired at baseline.

Figure 7: Effect of Sildenafil and Placebo on Maintenance of Erection by Baseline Score

The frequency of patients reporting improvement of erections in response to a global question in four of the sildenafil randomized, double-blind, parallel, placebo-controlled fixed dose studies (1797 patients) of 12 to 24 weeks duration is shown in Figure 8. These patients had erectile dysfunction at baseline that was characterized by median categorical scores of 2 (a few times) on principal IIEF questions. Erectile dysfunction was attributed to organic (58%; generally not characterized, but including diabetes and excluding spinal cord injury), psychogenic (17%), or mixed (24%) etiologies. Sixty-three percent, 74%, and 82% of the patients on 25 mg, 50 mg and 100 mg of sildenafil, respectively, reported an improvement in their erections, compared to 24% on placebo. In the titration studies (n=644) (with most patients eventually receiving 100 mg), results were similar.

Figure 8: Percentageof Patients Reportingan Improvement in Erections

The patients in the sildenafil studies had varying degrees of ED. One-third to one-half of the subjects in these studies reported successful intercourse at least once during a 4-week, treatment-free run-in period.

In many of the sildenafil studies, of both fixed dose and titration designs, daily diaries were kept by patients. In these studies, involving about 1600 patients, analyses of patient diaries showed no effect of sildenafil on rates of attempted intercourse (about 2 per week), but there was clear treatment-related improvement in sexual function: per patient weekly success rates averaged 1.3 on 50-100 mg of sildenafil vs 0.4 on placebo; similarly, group mean success rates (total successes divided by total attempts) were about 66% on sildenafil citrate vs about 20% on placebo.

During 3 to 6 months of double-blind treatment or longer-term (1 year), open-label sildenafil studies, few patients withdrew from active treatment for any reason, including lack of effectiveness. At the end of the long-term study, 88% of patients reported that sildenafil improved their erections.

Men with untreated ED had relatively low baseline scores for all aspects of sexual function measured (again using a 5-point scale) in the IIEF. Sildenafil improved these aspects of sexual function: frequency, firmness and maintenance of erections; frequency of orgasm; frequency and level of desire; frequency, satisfaction and enjoyment of intercourse; and overall relationship satisfaction.

One randomized, double-blind, flexible-dose, placebo-controlled sildenafil study included only patients with erectile dysfunction attributed to complications of diabetes mellitus (n=268). As in the other titration studies, patients were started on 50 mg and allowed to adjust the dose up to 100 mg or down to 25 mg of sildenafil; all patients, however, were receiving 50 mg or 100 mg at the end of the study. There were highly statistically significant improvements on the two principal IIEF questions (frequency of successful penetration during sexual activity and maintenance of erections after penetration) on sildenafil compared to placebo. On a global improvement question, 57% of sildenafil patients reported improved erections versus 10% on placebo. Diary data indicated that on sildenafil, 48% of intercourse attempts were successful versus 12% on placebo.

One randomized, double-blind, placebo-controlled, crossover, flexible-dose (up to 100 mg) sildenafil study of patients with erectile dysfunction resulting from spinal cord injury (n=178) was conducted. The changes from baseline in scoring on the two endpoint questions (frequency of successful penetration during sexual activity and maintenance of erections after penetration) were highly statistically significantly in favor of sildenafil. On a global improvement question, 83% of patients reported improved erections on sildenafil versus 12% on placebo. Diary data indicated that 59% of attempts at sexual intercourse were successful on sildenafil compared to 13% on placebo. Across all trials, sildenafil improved the erections of 43% of radical prostatectomy patients compared to 15% on placebo.

Subgroup analyses of responses to a global improvement question in patients with psychogenic etiology in two fixed-dose sildenafil studies (total n=179) and two sildenafil titration studies (total n=149) showed 84% of sildenafil patients reported improvement in erections compared with 26% of placebo. The changes from baseline in scoring on the two endpoint questions (frequency of successful penetration during sexual activity and maintenance of erections after penetration) were highly statistically significantly in favor of sildenafil .Diary data in two of the studies (n=178) showed rates of successful intercourse per attempt of 70% for sildenafil and 29% for placebo.

Efficacy Results in Subpopulations in Controlled Clinical Studies

A review of population subgroups in sildenafil studies demonstrated efficacy regardless of baseline severity, etiology, race and age. Sildenafil was effective in a broad range of ED patients, including those with a history of coronary artery disease, hypertension, other cardiac disease, peripheral vascular disease, diabetes mellitus, depression, coronary artery bypass graft (CABG), radical prostatectomy, transurethral resection of the prostate (TURP) and spinal cord injury, and in patients taking antidepressants/antipsychotics and antihypertensives/diuretics.

16 HOW SUPPLIED/STORAGE AND HANDLING

VYBRIQUE is supplied as oral films in individually sealed foil pouches in four dosage strengths. Each carton contains 4 or 8 pouches. The product is an opaque light blue, thin, flexible oral film with film imprint code, and characteristic lemon and grapefruit flavor with the following dimensions:

Strengths (mg) of sildenafil | Film Imprint Code | Film Dimensions (shape) | NDC for Carton of 4 Pouches | NDC for Carton of 8 Pouches
25 mg | S25 | 30 mm x 15 mm (rectangular) | 71858-0205-5 | 71858-0205-6
50 mg | S50 | 30 mm x 30 mm (square) | 71858-0210-5 | 71858-0210-6
75 mg | S75 | 30 mm x 45 mm (rectangular) | 71858-0215-5 | 71858-0215-6
100 mg | S100 | 45 mm x 40 mm (rectangular) | 71858-0220-5 | 71858-0220-6

Recommended Storage:Store at 20°C to 25°C (68°F to 77°F) with excursions permitted between 15°C to 30°C (59°F to 86°F) [see USP Controlled Room Temperature].

17 PATIENT COUNSELING INFORMATION

Advise the patient to read the FDA-approved patient labeling (Patient Information)

Administration Instructions

Advise patients to place VYBRIQUE directly onto the tongue where it will disintegrate and can then be swallowed with saliva without the need for water or other liquids. Advise patients not to cut or chew VYBRIQUE [see Dosage and Administration (2.4) ].

Nitrates

Physicians should discuss with patients the contraindication of VYBRIQUE with regular and/or intermittent use of nitric oxide donors, such as organic nitrates or organic nitrites in any form [see Contraindications (4.1)].

Guanylate Cyclase (GC) Stimulators

Physicians should discuss with patients the contraindication of VYBRIQUE with use of guanylate cyclase stimulators such as riociguat [see Contraindications (4.3)].

Concomitant Use with Drugs Which Lower Blood Pressure

Physicians should advise patients of the potential for VYBRIQUE to augment the blood pressure lowering effect of alpha-blockers and antihypertensive medications. Concomitant administration of VYBRIQUE and an alpha blocker may lead to symptomatic hypotension in some patients. Therefore, when VYBRIQUE is co-administered with alpha-blockers, patients should be stable on alpha-blocker therapy prior to initiating VYBRIQUE treatment and VYBRIQUE should be initiated at the lowest dose [see Warnings and Precautions (5.5)].

Cardiovascular Risk Considerations

Physicians should discuss with patients the potential cardiac risk of sexual activity in patients with preexisting cardiovascular risk factors. Patients who experience symptoms (e.g., angina pectoris, dizziness, nausea) upon initiation of sexual activity should be advised to refrain from further activity and should discuss the episode with their physician [see Warnings and Precautions (5.1)].

Sudden Loss of Vision

Physicians should advise patients to stop use of all PDE5 inhibitors, including VYBRIQUE and seek medical attention in the event of a sudden loss of vision in one or both eyes. Such an event may be a sign of non-arteritic anterior ischemic optic neuropathy (NAION), a cause of decreased vision including possible permanent loss of vision, that has been reported rarely post-marketing in temporal association with the use of all PDE5 inhibitors, including sildenafil. Physicians should discuss with patients the increased risk of NAION in individuals who have already experienced NAION in one eye. Physicians should also discuss with patients the increased risk of NAION among the general population in patients with a “crowded” optic disc, although evidence is insufficient to support screening of prospective users of PDE5 inhibitor, including VYBRIQUE, for this uncommon condition [see Warnings and Precautions (5.3), Adverse Reactions (6.2)].

Sudden Hearing Loss

Physicians should advise patients to stop taking PDE5 inhibitors, including VYBRIQUE and seek prompt medical attention in the event of sudden decrease or loss of hearing. These events, which may be accompanied by tinnitus and dizziness, have been reported in temporal association to the intake of PDE5 inhibitors, including VYBRIQUE. It is not possible to determine whether these events are related directly to the use of PDE5 inhibitors or to other factors [see Warnings and Precautions (5.4), Adverse Reactions (6.2)].

Priapism

Physicians should warn patients that prolonged erections greater than 4 hours and priapism (painful erections greater than 6 hours in duration) have been reported infrequently since market approval of sildenafil. In the event of an erection that persists longer than 4 hours, the patient should seek immediate medical assistance. If priapism is not treated immediately, penile tissue damage and permanent loss of potency may result [see Warnings and Precautions (5.2)].

Avoid Use with other PDE5 Inhibitors

Physicians should inform patients not to take VYBRIQUE with other PDE5 inhibitors, including pulmonary arterial hypertension (PAH) treatments containing sildenafil. The safety and efficacy of VYBRIQUE with other PDE5 inhibitors have not been studied [see Warnings and Precautions (5.7)].

Sexually Transmitted Disease

The use of VYBRIQUE offers no protection against sexually transmitted diseases. Counseling of patients about the protective measures necessary to guard against sexually transmitted diseases, including the Human Immunodeficiency Virus (HIV), should be considered [see Warnings and Precautions (5.9)].

Distributed by:
IBSA Pharma Inc,
Parsippany, NJ 07054 USA

Patient Information
VYBRIQUETM (vī-BRĒK)
(sildenafil)
Oral Film

What is the most important information I should know about VYBRIQUE?
VYBRIQUEcan cause your blood pressure to drop suddenly to an unsafe level if it is taken with certain other medicines.Do not take VYBRIQUE if you take any other medicines called nitrates. Nitrates are used to treat chest pain (angina). A sudden drop in blood pressure can cause you to feel dizzy, faint, or have a heart attack or stroke.
Do not take VYBRIQUE if you take medicines called guanylate cyclase stimulators which include:

- Riociguat a medicine that treats pulmonary arterial hypertension and chronic thromboembolic pulmonary hypertension.

Tell all your healthcare providers that you take VYBRIQUE. If you need emergency medical care for a heart problem, it will be important for your healthcare provider to know when you last took VYBRIQUE.
Stop sexual activity and get medical help right away if you get symptoms such as chest pain, dizziness, or nausea during sex. Sexual activity can put an extra strain on your heart, especially if your heart is already weak from a heart attack or heart disease. VYBRIQUE does not protect you or your partner from getting sexually transmitted diseases, including Human Immunodeficiency Virus (HIV).

What is VYBRIQUE?
VYBRIQUE is a prescription medicine used to treat erectile dysfunction (ED).
VYBRIQUE is not for use in women or children.
It is not known if VYBRIQUE is safe and effective in women or children under 18 years of age.

Do not take VYBRIQUEif you:

- take medicines called nitrates.
- take any medicines called guanylate cyclase stimulators.
- are allergic to sildenafil or any of the ingredients in VYBRIQUE. See the end of this Patient information leaflet for a complete list of ingredients in VYBRIQUE.

Before taking VYBRIQUE, tell your healthcare provider about all of your medical conditions, including if you:

- have or have had heart problems such as a heart attack, irregular heartbeat, angina, chest pain, narrowing of the aortic valve or heart failure.
- have had heart surgery within the last 6 months.
- have pulmonary hypertension.
- have had a stroke.
- have low blood pressure, or high blood pressure that is not controlled.
- have a deformed penis shape.
- have had an erection that lasted for more than 4 hours.
- have problems with your blood cells such as sickle cell anemia, multiple myeloma, or leukemia.
- have retinitis pigmentosa, a rare genetic (runs in families) eye disease.
- have ever had severe vision loss, including an eye problem called non-arteritic anterior ischemic optic neuropathy (NAION).
- have bleeding problems.
- have or have had stomach ulcers.
- have liver problems.
- have kidney problems or are having kidney dialysis.

Tell your healthcare provider about all the medicines you take,including prescription and over-the-counter medicines, vitamins, and herbal supplements.
VYBRIQUE may affect the way other medicines work, and other medicines may affect the way VYBRIQUE works causing side effects. Especially tell your healthcare provider if you take any of the following:

- medicines called nitrates (see “What is the most important information I should know about VYBRIQUE?”)
- medicines called guanylate cyclase stimulators, such as riociguat (see “ What is the most important information I should know about VYBRIQUE?”)
- medicines called alpha blockers such as doxazosin. Alpha-blockers are sometimes prescribed for prostate problems or high blood pressure. In some patients, the use of VYBRIQUE with alpha-blockers can lead to a drop-in blood pressure or to fainting.
- medicines called HIV protease inhibitors, such as ritonavir and saquinavir.
- some types of oral antifungal medicines, such as ketoconazole and itraconazole.
- some types of antibiotics, such as erythromycin.
- other medicines that treat high blood pressure.
- other medicines or treatments for ED.

Ask your healthcare provider or pharmacist for a list of these medicines, if you are not sure.
Know the medicines you take. Keep a list of them to show to your healthcare provider and pharmacist when you get a new medicine.

How should I take VYBRIQUE?

- Take VYBRIQUE exactly as your healthcare provider tells you to take it.
- Your healthcare provider will tell you how much VYBRIQUE to take and when to take it.
- Your healthcare provider may change your dose if needed.
- Take VYBRIQUE by mouth about 1 hour before sexual activity. You may take VYBRIQUE between 30 minutes to 4 hours before sexual activity if needed.
- VYBRIQUE can be taken with or without food.
- Do not cut or chew VYBRIQUE.
- Do nottake VYBRIQUE more than 1 time a day.
- If you take too much VYBRIQUE, call your healthcare provider or go to the nearest hospital emergency room right away.

Instructions for Use
Important information you need to know before using VYBRIQUE

- Do not remove the film from the pouch unless ready for immediate use.
- Do not handle the oral film with wet hands.

a) Take the pouch and locate the notch on the side of the pouch.

b) Gently tear along the dotted line to open the pouch.

c) Gently peel both parts of the pouch. Now you can hold each side of the pouch between your thumb and your index finger.

d) Take the oral film with dry fingers out of the pouch and put it onto your tongue. It will dissolve in your mouth and can be swallowed with saliva.

What are the possible side effects of VYBRIQUE?
VYBRIQUEcan cause serious side effects including:

- See “What is the most important information I should know about VYBRIQUE?”
- an erection that will not go away (priapism).If you have an erection that lasts more than 4 hours, get medical help right away. If it is not treated right away, priapism can permanently damage your penis.
- sudden vision loss in one or both eyes.Sudden vision loss in 1 or both eyes can be a sign of a serious eye problem called non-arteritic anterior ischemic optic neuropathy (NAION). It is uncertain whether PDE5 inhibitors directly cause the vision loss. Stop taking VYBRIQUE and call your healthcare provider right away if you have sudden vision loss in 1 or both eyes.
- sudden hearing decrease or hearing loss.Some people may also have ringing in their ears (tinnitus) or dizziness. If you have these symptoms, stop taking VYBRIQUE and contact a healthcare provider right away.

The most common side effects of VYBRIQUEare:

- headache
- flushing
- upset stomach
- stuffy or runny nose
- dizziness

Other side effects include:

- abnormal vision, such as changes in color and blurred vision
- back pain
- muscle pain
- nausea
- rash

Tell your healthcare provider if you have any side effect that bothers you or does not go away.
These are not all of the possible side effects of VYBRIQUE. Call your doctor for medical advice about side effects. You may report side effects to FDA at 1-800-FDA-1088.

How should I store VYBRIQUE?

- Store VYBRIQUE at room temperature between 68°F to 77°F (20°C to 25°C).

Keep VYBRIQUEand all medicines out of the reach of children.

General information about the safe and effective use of VYBRIQUE.
Medicines are sometimes prescribed for purposes other than those listed in a Patient Information leaflet. Do not use VYBRIQUE for a condition for which it was not prescribed. Do not give VYBRIQUE to other people, even if they have the same symptoms that you have. It may harm them. You can ask your healthcare provider or pharmacist for information about VYBRIQUE that is written for health professionals.

What are the ingredients in VYBRIQUE?
Active ingredient:sildenafil
Inactive ingredients: Blue Videojet ink, FD&C Blue No.2, glycerin, grapefruit flavor, lemon flavor, maltodextrin, polysorbate 20, polyvinyl acetate dispersion, propylene glycol monocaprylate, sucralose, titanium dioxide.
Contains no ingredient made from a gluten-containing grain (wheat, barley or rye).
Manufactured by: ALTERGON Italia Srl, via Zona Industriale, Morra de Sanctis, Avellino 83040, Italy
Manufactured for: IBSA Institut Biochimique SA, CH-6912 Pazzallo, Switzerland
Distributed by: IBSA Pharma Inc, Parsippany, NJ 07054 USA

This Patient Information has been approved by the U.S. Food and Drug Administration Approved: 12/2025

PRINCIPAL DISPLAY PANEL

NDC 71858-0205-5
Vybrique
(Sildenafil) Oral film
25 mg per oral film
4 oral films
Rx

PRINCIPAL DISPLAY PANEL

NDC 71858-0205-6
Vybrique
(Sildenafil) Oral film
25 mg per oral film
8 oral films
Rx

PRINCIPAL DISPLAY PANEL

NDC 71858-0210-5
Vybrique
(Sildenafil) Oral film
50 mg per oral film
4 oral films
Rx

PRINCIPAL DISPLAY PANEL

NDC 71858-0210-6
Vybrique
(Sildenafil) Oral film
50 mg per oral film
8 oral films
Rx

PRINCIPAL DISPLAY PANEL

NDC 71858-0215-5
Vybrique
(Sildenafil) Oral film
75 mg per oral film
4 oral films
Rx

PRINCIPAL DISPLAY PANEL

NDC 71858-0215-6
Vybrique
(Sildenafil) Oral film
75 mg per oral film
8 oral films
Rx

PRINCIPAL DISPLAY PANEL

NDC 71858-0220-5
Vybrique
(Sildenafil) Oral film
100 mg per oral film
4 oral films
Rx

PRINCIPAL DISPLAY PANEL

NDC 71858-0220-6
Vybrique
(Sildenafil) Oral film
100 mg per oral film
8 oral films
Rx